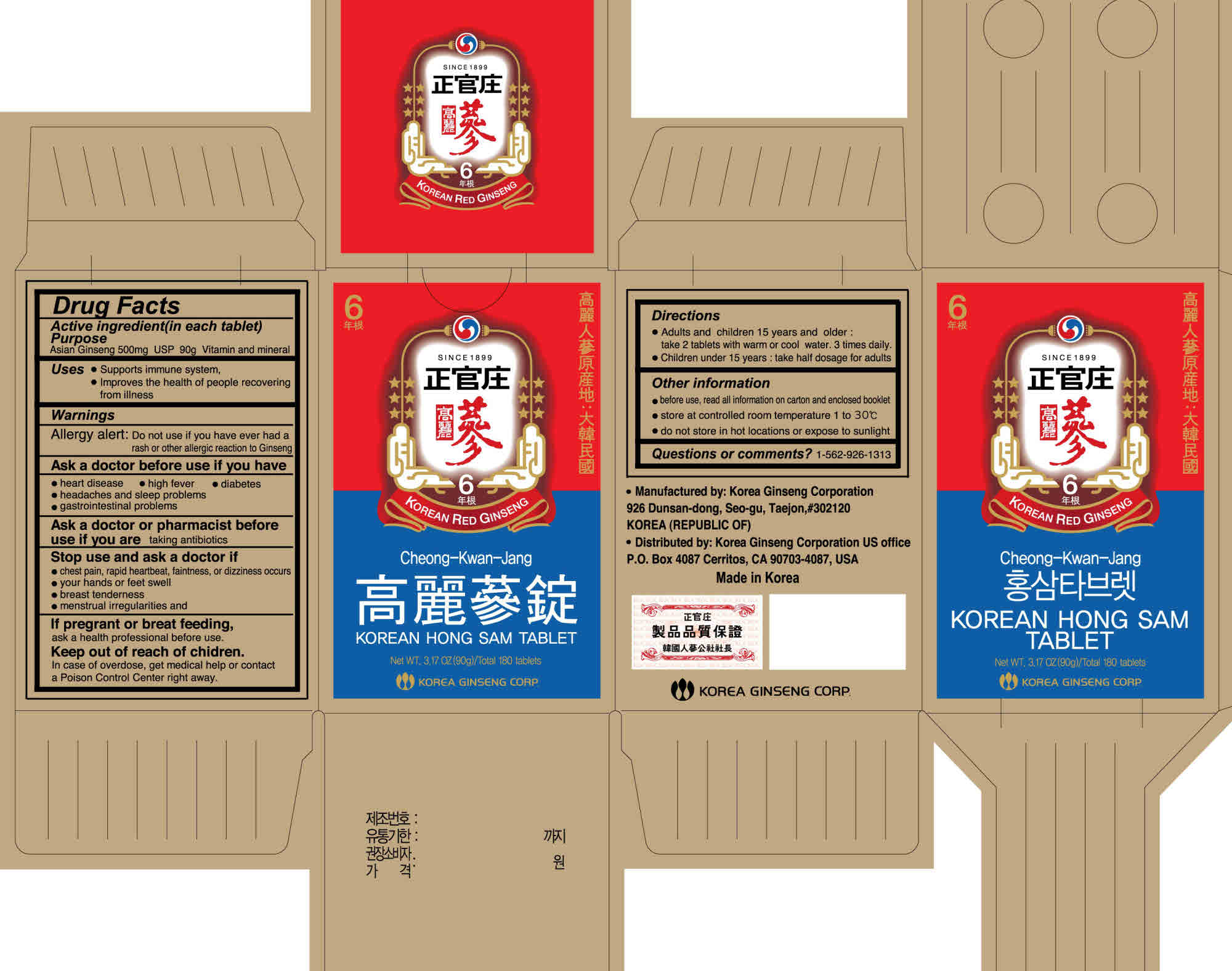 DRUG LABEL: Cheong-Kwan-Jang Korean HongSam
NDC: 51918-1002 | Form: TABLET
Manufacturer: Korea Ginseng Corporation
Category: otc | Type: HUMAN OTC DRUG LABEL
Date: 20110224

ACTIVE INGREDIENTS: ASIAN GINSENG 500 mg/90000 mg
INACTIVE INGREDIENTS: WATER

Cheong-Kwan-Jang Korean HongSam Tablet

Drug Facts

Active Ingredient
Asian Ginseng 500mg

Purpose

vitamin and mineral

Keep out of Reach of Children

Stop use and ask a doctor if
- chest pain, rapid heartbeat, or dizziness occurs
- your hands or feet swell
- breast tenderness
- menstrual irregularities

- If pregnant or breast feeding, ask a health professional before use.

- Keep out of reach of children. In case of overdose, get medical help or contact a Poison Control Center right away.

Indication & Usage

Uses
- Supports immune system
- Improves the health of people recovering from illness.

Other information
- before use, read all information on carton and enclosed booklet.
- store at controlled room temperature 1 to 30 ℃
- do not store in hot location or expose to sunlight.

Warnings

Allergy alert: Do not use if you have ever had a rash or other allergic reaction to Ginseng
Ask a doctor before use if you have
-heart disease
-high fever
-diabetes
-headaches and sleep problems
-gastrointestinal problems
Ask a doctor or pharmacist before use if you are taking antibiotics.

Dosage & Administraion

Adults and children 15 years and older;
take 2 capsules with warm or cool water. 3 times daily.
Children under 15 years ;
take half dosage for adults

Inactive Ingredient

Asian Ginseng, Water

Korea Ginseng Corporation

Cheong-Kwan-Jang Korean HongSam Tablet

Net WT. 3.17 OZ (90g) total 180 tablets